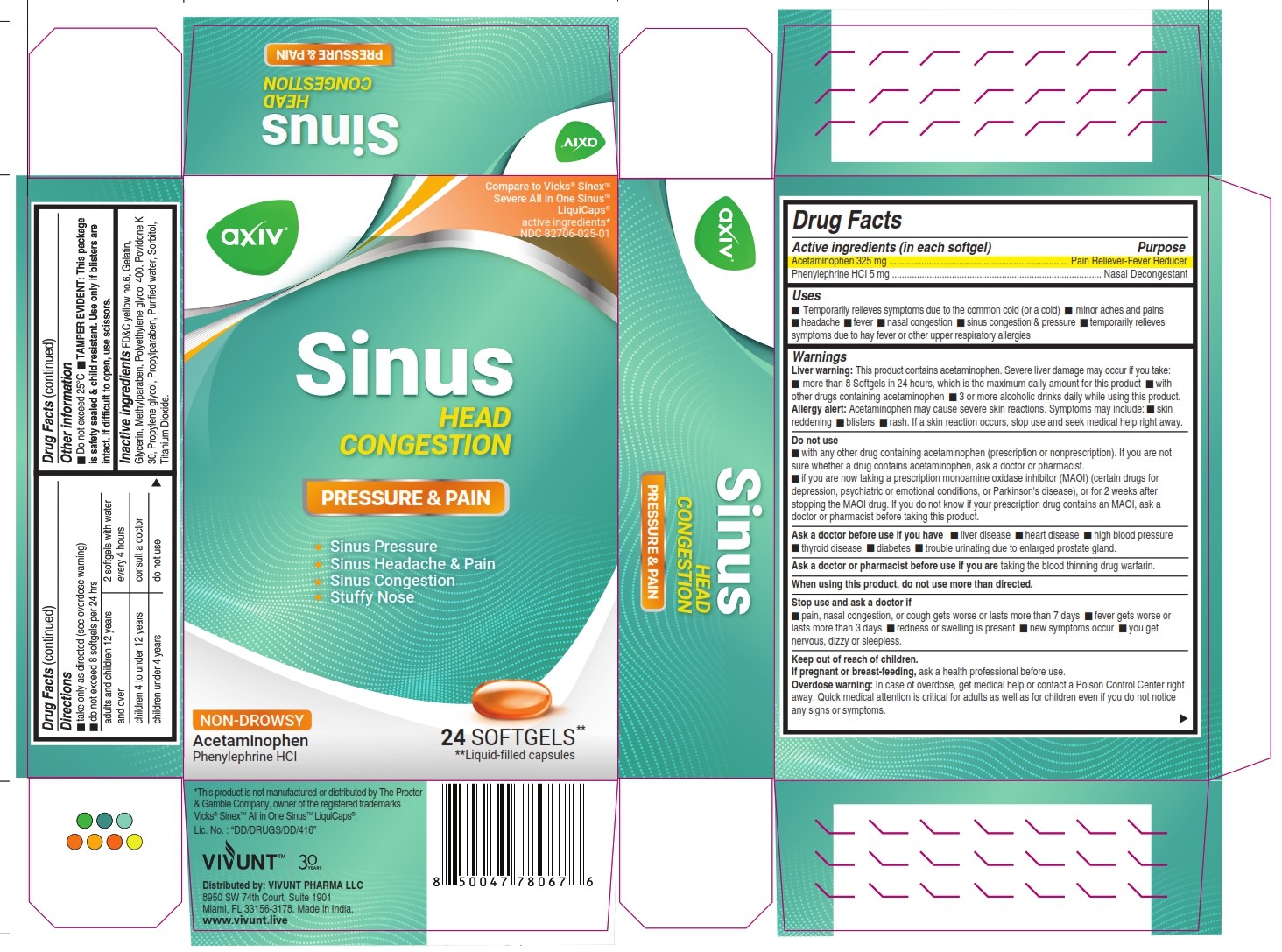 DRUG LABEL: Sinus Head Congestion
NDC: 82706-025 | Form: CAPSULE, LIQUID FILLED
Manufacturer: VIVUNT PHARMA LLC
Category: otc | Type: HUMAN OTC DRUG LABEL
Date: 20250318

ACTIVE INGREDIENTS: ACETAMINOPHEN 325 mg/1 1; PHENYLEPHRINE HYDROCHLORIDE 5 mg/1 1
INACTIVE INGREDIENTS: PROPYLPARABEN; TITANIUM DIOXIDE; METHYLPARABEN; POVIDONE K30; WATER; PROPYLENE GLYCOL; SORBITOL; POLYETHYLENE GLYCOL 400; GELATIN; FD&C YELLOW NO. 6; GLYCERIN

AXIV Sinus Head Congestion

Active ingredients

Purpose

Active ingredients (in each softgel) | Purpose
Acetaminophen 325 mg | Pain Reliever-Fever reducer
Phenylephrine HCl 5 mg | Nasal Descongestant

Uses

- Temporarily relieves symptoms due to the common cold (or a cold)
- minor aches and pains
- headache
- fever
- nasal congestion
- sinus congestion & pressure
- temporarily relieves symptoms due to hay fever or other respiratory allergies

Warnings

Liver warning: This product contains acetaminophen. Severe liver damage may occur if you take:

- more than 8 Softgels in 24 hours, which is the maximum daily amount for this product
- with other drugs containing acetaminophen
- 3 or more alcoholic drinks daily while using this product

Allergy alert: Acetaminophen may cause severe skin reactions. Symptomsmay include:

- skin reddening
- blisters
- rash.
- If a skin reaction occurs, stop use and seek medical help right away.

Do not use

- with any other drug containing acetaminophen (prescription or nonprescription). If you are not sure whether a drug contains acetaminophen, ask a doctor or pharmacist
- if you are now taking a prescription monoamine oxidase inhibitor (MAOI) (certain drugs for depression, psyciatric or emotional conditions, or Parkinson´s disease), or for 2 weeks after stopping the MAOI drug. If you do not know if your prescription drug contains an MAOI, ask a doctor or pharmacist before taking this product.

Ask a doctor or pharmacist before use if you are

Taking the blood thinning drug warfarin.

Ask a doctor before use if you have

- liver disease
- heart disease
- hight blood pressure
- thyroid disease
- diabetes
- trouble urinating due to enlarged prostate gland

When using this product

do not use more than directed

Stop use and ask a doctor if

- pain, nasal congestion, or cough gets worse or lasts more than 7 days
- fever gets worse or lasts more than 3 days
- redness or swelling is present
- new symptoms occur
- you get nervous, dizzy or sleepless

Keep out of reach of children

If pregnant or breast-feeding,

ask a health professional before use.

Overdose warning:

In case of overdose, get medical help or contact a Poison Control Center right away. Quick medical attention is critical for adults as well as for children even if you do not notice any signs or symptoms.

Directions

- take only as directed (see overdose warning)
- do not exceed 8 softgels per 24 hrs

adults and children 12 years and over | 2 softgels with water every 4 hours
children 4 to under 12 years | consult a doctor
children under 4 years | do not use

Other information

Do not exceed 25°C

TAMPER EVIDENT:This package is safety sealed & child resistant. Use only if blisters are intact. If difficult to open, use scissors.

Inactive ingredients

FD&C yellow no.6, Gelatin, Glycerin, Methylparaben, Polyethylene glycol 400, Povidone K 30, Propylene glycol, Propyparaben, Purified water, Sorbitol, Titanium Dioxide.

PACKAGE LABEL

Compare to Vicks® Sinex TM

Severe All in One Sinus TM

Liquicaps®

active ingredients*

NDC 82706-025-01

Sinus

HEAD CONGESTION

PRESSURE & PAIN

-Sinus Pressure

-Sinus Headache & Pain

-Sinus Cingestion

-Stuffy Nose

NON-DROWSY

Acetaminophen

Phenylephrine HCl

24 SOFTGELS**

**Liquid-filled capsules

*This product is not manufactured or distributed by The Procter & Gamble Company, owner of the registered trademarks Vicks® Sinex TM All in One Sinus TM LiquiCaps ®.

Lic. No. :"DD/DRUGS/DD/416"

VIVUNT TM

Distributed by: VIVUNT PHARMA LLC

8950 SW 74th Court, Suite 1901

Miami, FL 33156-3178. Made in India.

www.vivunt.live